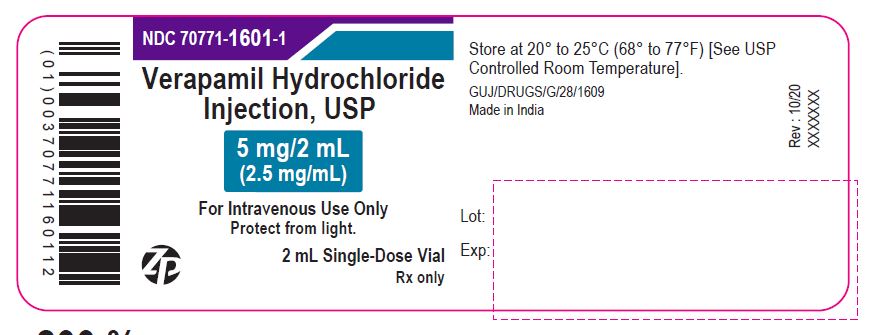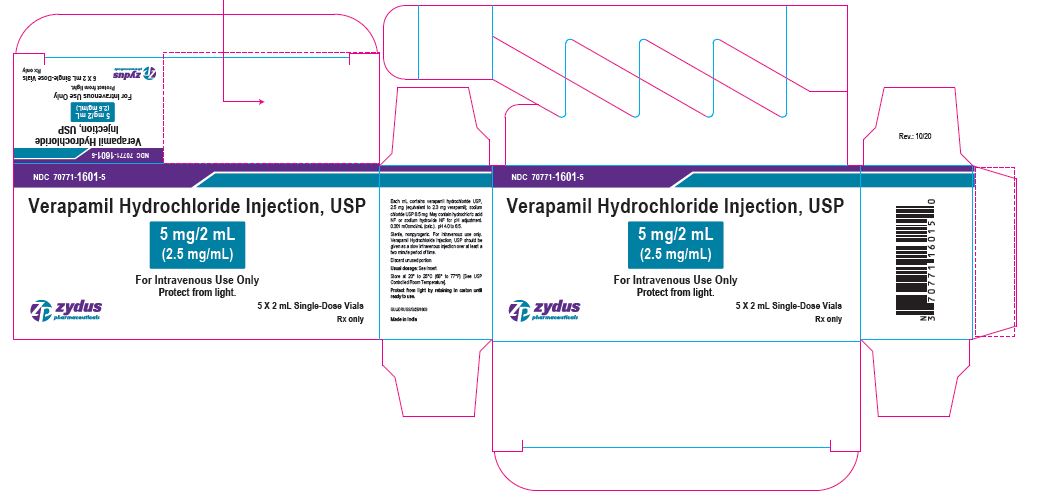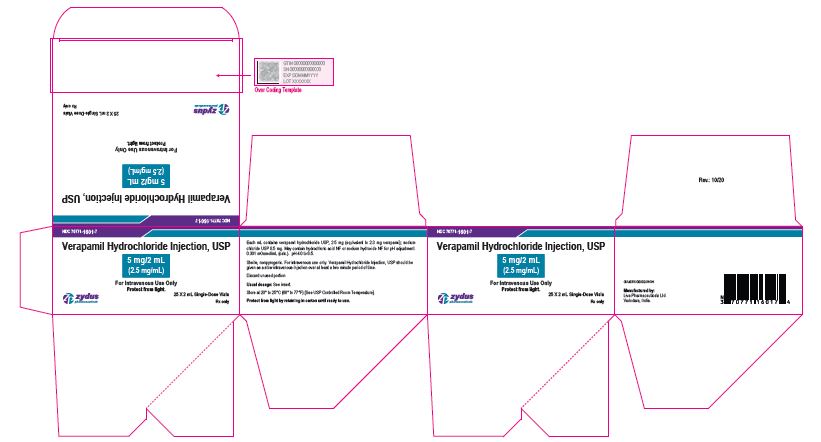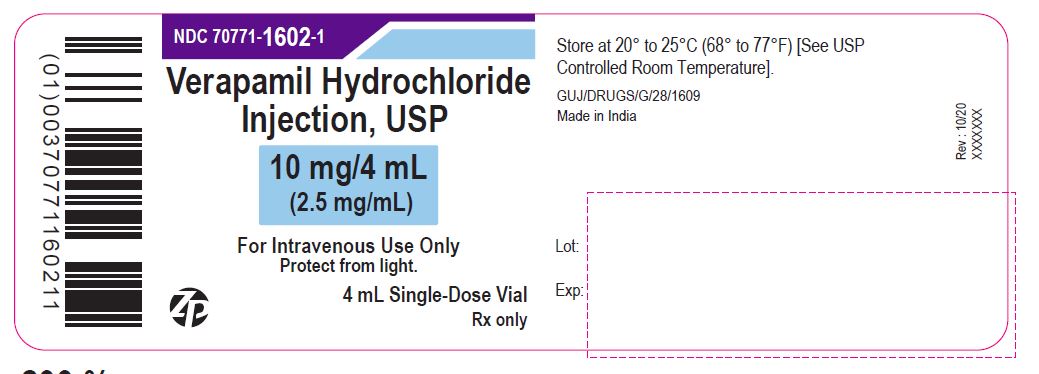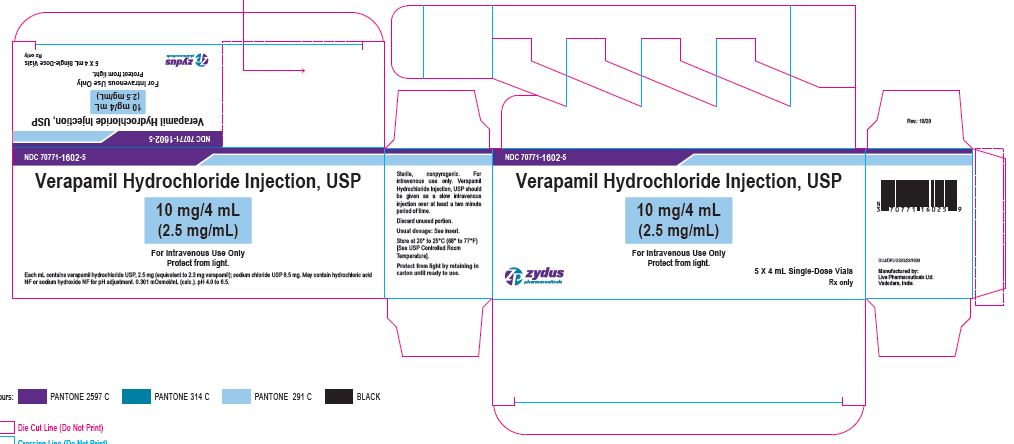 DRUG LABEL: Verapamil Hydrochloride
NDC: 70771-1601 | Form: INJECTION, SOLUTION
Manufacturer: Zydus Lifesciences Limited
Category: prescription | Type: HUMAN PRESCRIPTION DRUG LABEL
Date: 20221105

ACTIVE INGREDIENTS: VERAPAMIL HYDROCHLORIDE 2.5 mg/1 mL
INACTIVE INGREDIENTS: SODIUM CHLORIDE 8.5 mg/1 mL; WATER; HYDROCHLORIC ACID; SODIUM HYDROXIDE

Verapamil Hydrochloride Injection, USP
Single-Dose Fliptop Vial
Protect from light.
Rx only

PACKAGE LABEL.PRINCIPAL DISPLAY PANEL

NDC 70771-1601-1

Verapamil Hydrochloride Injection, USP

5 mg/2 mL

(2.5 mg/mL)

For Intravenous Use Only

Protect from light.

2 mL Single-Dose Vial

Rx only

NDC 70771-1601-5

Verapamil Hydrochloride Injection, USP

5 mg/2 mL

(2.5 mg/mL)

For Intravenous Use Only

Protect from light.

5 X 2 mL Single-Dose Vials

Rx only

NDC 70771-1601-7

Verapamil Hydrochloride Injection, USP

5 mg/2 mL

(2.5 mg/mL)

For Intravenous Use Only

Protect from light.

25 X 2 mL Single-Dose Vials

Rx only

PACKAGE LABEL.PRINCIPAL DISPLAY PANEL

NDC 70771-1602-1

Verapamil Hydrochloride Injection, USP

10 mg/4 mL

(2.5 mg/mL)

For Intravenous Use Only

Protect from light.

4 mL Single-Dose Vial

Rx only

NDC 70771-1602-5

Verapamil Hydrochloride Injection, USP

10 mg/4 mL

(2.5 mg/mL)

For Intravenous Use Only

Protect from light.

5 X 4 mL Single-Dose Vials

Rx only